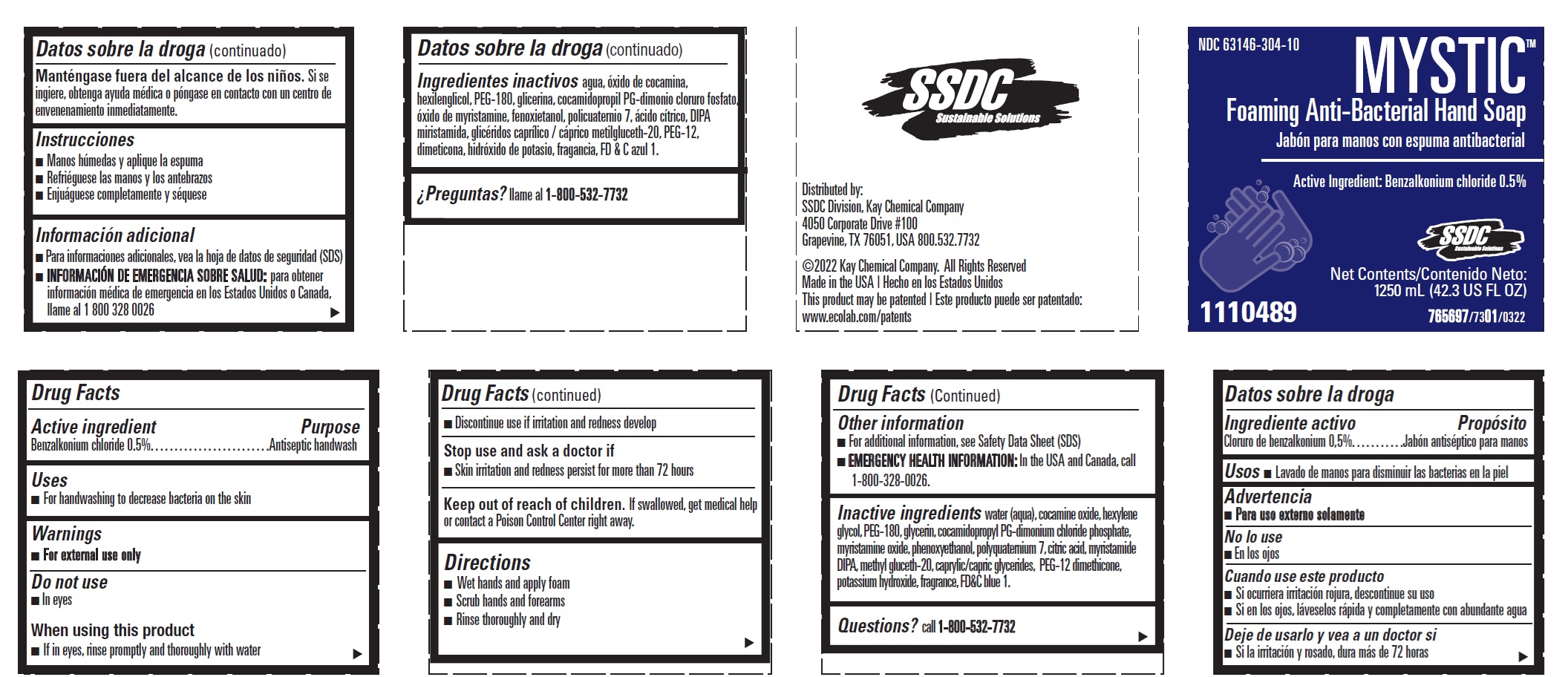 DRUG LABEL: MYSTIC FOAMING ANTI-BACTERIAL HANDSOAP
NDC: 47593-681 | Form: SOLUTION
Manufacturer: Ecolab Inc.
Category: otc | Type: HUMAN OTC DRUG LABEL
Date: 20251231

ACTIVE INGREDIENTS: BENZALKONIUM CHLORIDE 5 mg/1 mL
INACTIVE INGREDIENTS: FD&C BLUE NO. 1; POTASSIUM HYDROXIDE; PEG-12 DIMETHICONE (300 CST); GLYCERYL MONO- AND DICAPRYLOCAPRATE; METHYL GLUCETH-20; MYRISTIC DIISOPROPANOLAMIDE; ANHYDROUS CITRIC ACID; POLYQUATERNIUM-7 (70/30 ACRYLAMIDE/DADMAC; 1600000 MW); PHENOXYETHANOL; MYRISTAMINE OXIDE; COCAMIDOPROPYL PG-DIMONIUM CHLORIDE PHOSPHATE; GLYCERIN; POLYETHYLENE GLYCOL 8000; HEXYLENE GLYCOL; WATER; COCAMINE OXIDE

Drug Facts

Active Ingredient

Benzalkonium chloride 0.5%

Purpose

Antiseptic handwash

Uses

- for handwashing to decrease bacteria on the skin

Warnings

- For external use only

Do not use

- in eyes

When using the product

- if in eyes, rinse promptly and thoroughly with water
- discontinue use if irritation and redness develop

Stop use and ask a docotr if

- Skin irritation or redness occurs for more than 72 hours

Keep out of reach of children. If swallowed, get medical help or contact a Poison Control Center right away.

Directions

- Wet hands and apply foam
- Scrub hands and forearms
- Rinse thoroughly and dry

Other information

- for additional information, see Safety Data Sheet (SDS)
- EMERGENCY HEALTH INFORMATION: In the USA and Canada, call 1-800-328-0026

INACTIVE INGREDIENT

Inactive ingredients water (aqua), cocamine oxide, hexylene glycol, PEG-180, glycerin, cocamidopropyl PG-dimonium chloride phosphate, myristamine oxide, phenoxyethanol, polyquaternium 7, citric acid, myristamide DIPA, methyl gluceth-20, caprylic/capric glycerides, PEG-12 dimethicone, potassium hydroxide, fragrance, FD&C blue 1

Questions? Call 1-800-532-7732

Representative Label and Principal Display Panel

NDC 63146-304-10

MYSTIC™

Foaming Anti-Bacterial Hand Soap

Active Ingredient: Benzalkonium chloride 0.5%

1110489

Net Content: 1250 mL (42.3 US FL OZ)

Distributed by:

SSDC Division, Kay Chemical Company

4050 Corporate Drive, #100

Grapevine, Texas 76051, USA 800.532.7732

©2022 Kay Chemical Company All Rights Reserved

765697/7301/0322